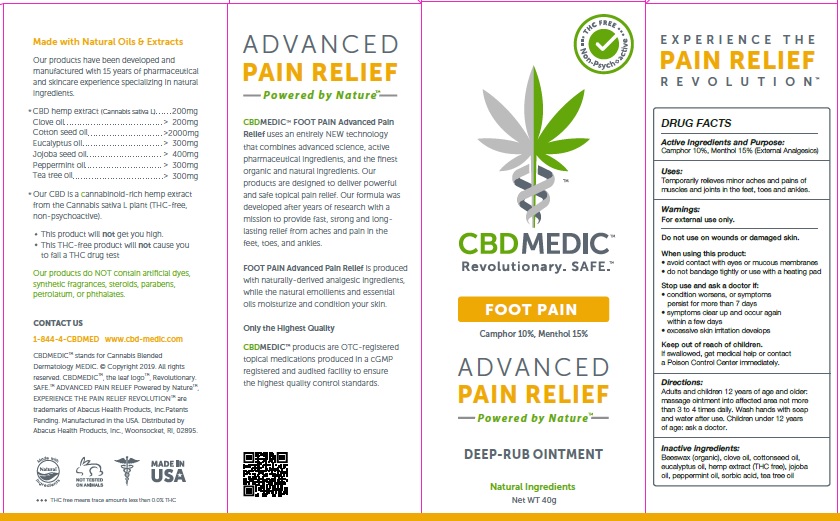 DRUG LABEL: CBDMEDIC Foot Pain Relief
NDC: 24909-739 | Form: OINTMENT
Manufacturer: AIDANCE SKINCARE & TOPICAL SOLUTIONS, LLC
Category: otc | Type: HUMAN OTC DRUG LABEL
Date: 20190306

ACTIVE INGREDIENTS: CAMPHOR (SYNTHETIC) 100 mg/1 g; MENTHOL 150 mg/1 g
INACTIVE INGREDIENTS: WHITE WAX; CLOVE OIL; COTTONSEED OIL; EUCALYPTUS OIL; HEMP; JOJOBA OIL; PEPPERMINT OIL; SORBIC ACID; TEA TREE OIL

CBDMEDIC Foot Pain Relief

Active Ingredients and Purpose

Camphor 10%, Menthol 15% (External Analgesics)

Uses

Temporarily relieves minor aches and pains of muscles and joints in the feet, toes and ankles.

Warnings

For external use only. Do not use on wounds or damaged skin. When using this product: • avoid contact with eyes or mucous membranes • do not bandage tightly or use with a heating pad. Stop use and ask a doctor if: • condition worsens, or symptoms persist for more than 7 days • symptoms clear up and occur again within a few days • excessive skin irritation develops.

Keep out of reach of children

If swallowed, get medical help or contact a Poison Control Center immediately.

Directions

Adults and children 12 years of age and older: massage ointment into affected area not more than 3 to 4 times daily. Wash hands with soap and water after use. Children under 12 years of age: ask a doctor.

Inactive ingredients

Beeswax (organic), clove oil, cottonseed oil, eucalyptus oil, hemp extract (THC free), jojoba oil, peppermint oil, sorbic acid, tea tree oil